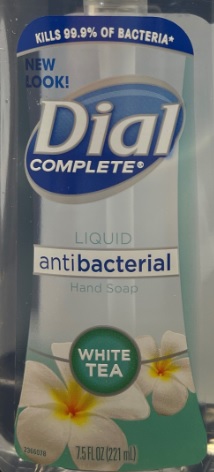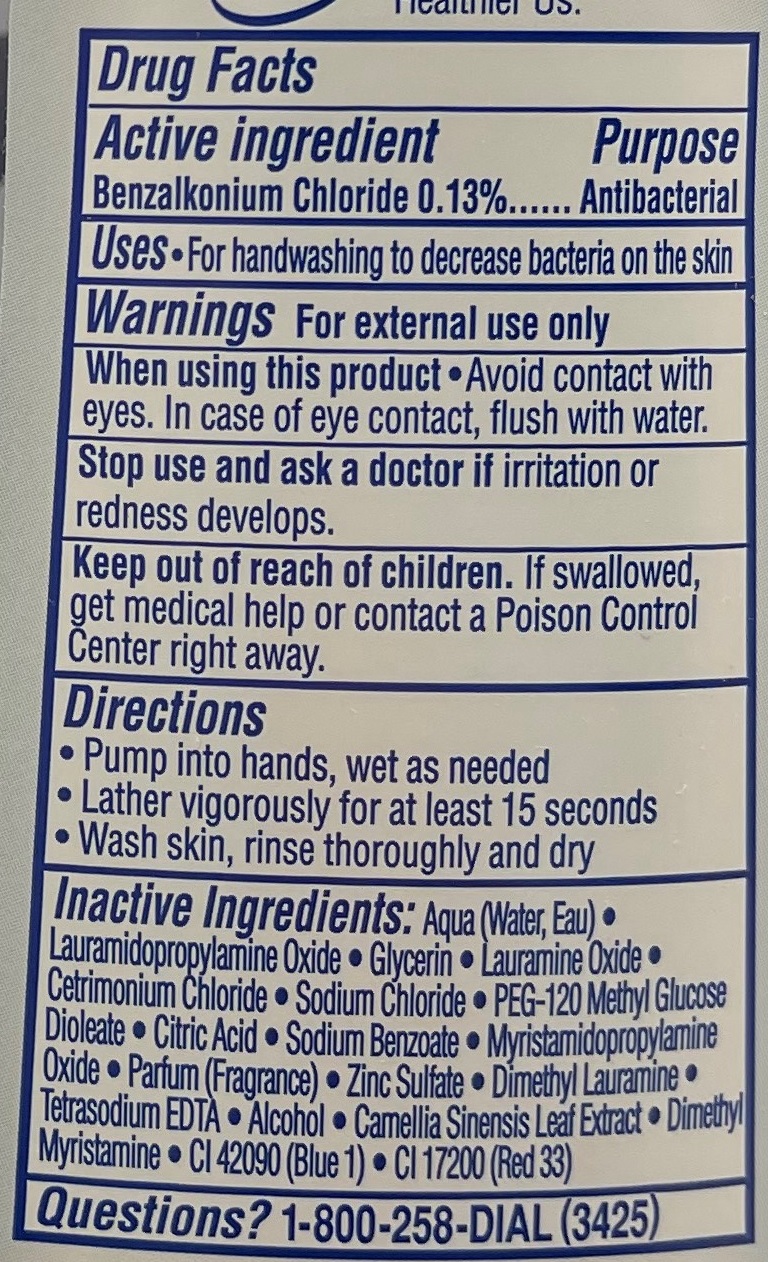 DRUG LABEL: Dial Antimicrobial
NDC: 57702-500 | Form: LIQUID
Manufacturer: Bocchi Laboratories
Category: otc | Type: HUMAN OTC DRUG LABEL
Date: 20210111

ACTIVE INGREDIENTS: BENZALKONIUM CHLORIDE 13 g/100 mL
INACTIVE INGREDIENTS: DIMETHYL LAURAMINE; ANHYDROUS CITRIC ACID; LAURAMIDOPROPYLAMINE OXIDE; GLYCERIN; CETRIMONIUM CHLORIDE; SODIUM CHLORIDE; WATER; DIMETHYL MYRISTAMINE; SODIUM BENZOATE; MYRISTAMIDOPROPYLAMINE OXIDE; ALCOHOL; LAURAMINE OXIDE; PEG-120 METHYL GLUCOSE DIOLEATE; FD&C BLUE NO. 1; D&C RED NO. 33; CHAMOMILE; ZINC SULFATE; EDETATE SODIUM

Dial Antimicrobial

Active Ingredient
Benzalkonium Chloride 0.13%

Purpose
Antibacterial

Uses

- For handwashing to decrease bacteria on the skin

Warnings
For external use only.

Stop use and ask a doctor if

- if irritation or redness develops

Keep out of reach of children.
If swallowed, get medical help or contact a Poison Control center right away.

Directions

- Pump into hands, wet as needed
- Lather vigorously for at least 15 seconds
- Wash skin, rinse thouroughly and dry

INACTIVE INGREDIENT

Aqua (Water, Eau), Lauramidopropylamine Oxide, Glycerin, Lauramine Oxide, Cetrimonium Chloride, Sodium Chloride, PEG-120 Methyl Glucose Dioleate, Citric Acid, Sodium Benzoate, Myristamidopropylamine Oxide, Parfum (Fragrance), Zinc Sulfate, Dimethyl Lauramine, Tetrasodium EDTA, Alcohol, Camellia Sinensis Leaf Extract, Dimethyl Myristamine, CI 42090 (Blue 1), CI 17200 (Red 33)

Questions?
Call 1-800-258-DIAL (3425)

When using this product

Avoid contact with eyes, in case of eye contact, flush with water